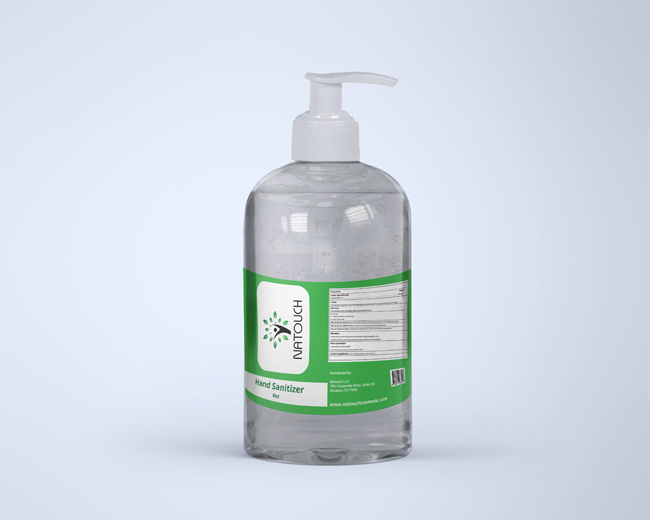 DRUG LABEL: natouch
NDC: 79073-006 | Form: SOAP
Manufacturer: Natouch LLC
Category: otc | Type: HUMAN OTC DRUG LABEL
Date: 20260211

ACTIVE INGREDIENTS: MICONAZOLE 1.2 g/120 g
INACTIVE INGREDIENTS: SODIUM PALMATE 112.92 g/120 g; WATER 1.8 g/120 g; LAVENDER OIL 0.6 g/120 g; EUCALYPTUS OIL 0.6 g/120 g; TEA TREE OIL 0.6 g/120 g; INDIGOTINDISULFONATE SODIUM 0.06 g/120 g; FD&C YELLOW NO. 5 0.06 g/120 g; SODIUM CHLORIDE 0.48 g/120 g; GLYCERIN 1.8 g/120 g

Natouch Antifungal Soap Medicated

This is a hand sanitizer manufactured according to the Temporary Policy for Preparation of Certain Alcohol-Based Hand Sanitizer Products During the Public Health Emergency (CoViD-19); Guidance for Industry.

The hand sanitizer is manufactured using only the following United States Pharmacopoeia (USP) grade ingredients in the preparation of the product (percentage in final product formulation) consistent with World Health Organization (WHO) recommendations:

1. Alcohol (ethanol) (USP or Food Chemical Codex (FCC) grade) (80%, volume/volume (v/v)) in an aqueous solution denatured according to Alcohol and Tobacco Tax and Trade Bureau regulations in 27 CFR part 20.
2. Glycerol (1.45% v/v).
3. Hydrogen peroxide (0.125% v/v).
4. Sterile distilled water or boiled cold water.

The firm does not add other active or inactive ingredients. Different or additional ingredients may impact the quality and potency of the product.

Active Ingredient(s)

Alcohol 70% v/v. Purpose: Antiseptic

Purpose

Antiseptic, Hand Sanitizer

Use

Hand Sanitizer to help reduce bacteria that potentially can cause disease. For use when soap and water are not available.

Warnings

For external use only. Flammable. Keep away from heat or flame

Do not use

- in children less than 2 months of age
- on open skin wounds

When using this product keep out of eyes, ears, and mouth. In case of contact with eyes, rinse eyes thoroughly with water.
Stop use and ask a doctor if irritation or rash occurs. These may be signs of a serious condition.
Keep out of reach of children. If swallowed, get medical help or contact a Poison Control Center right away.

Stop use and ask a doctor if irritation or rash occurs. These may be signs of a serious condition.

Keep out of reach of children. If swallowed, get medical help or contact a Poison Control Center right away.

Directions

- Place enough product on hands to cover all surfaces. Rub hands together until dry.
- Supervise children under 6 years of age when using this product to avoid swallowing.

Other information

- Store between 15-30C (59-86F)
- Avoid freezing and excessive heat above 40C (104F)

Inactive ingredients

glycerin, lavender oil, carbomer, purified water USP

Package Label - Principal Display Panel

NDC: Natouch Antifungal Wipes Plus 79073-004-80